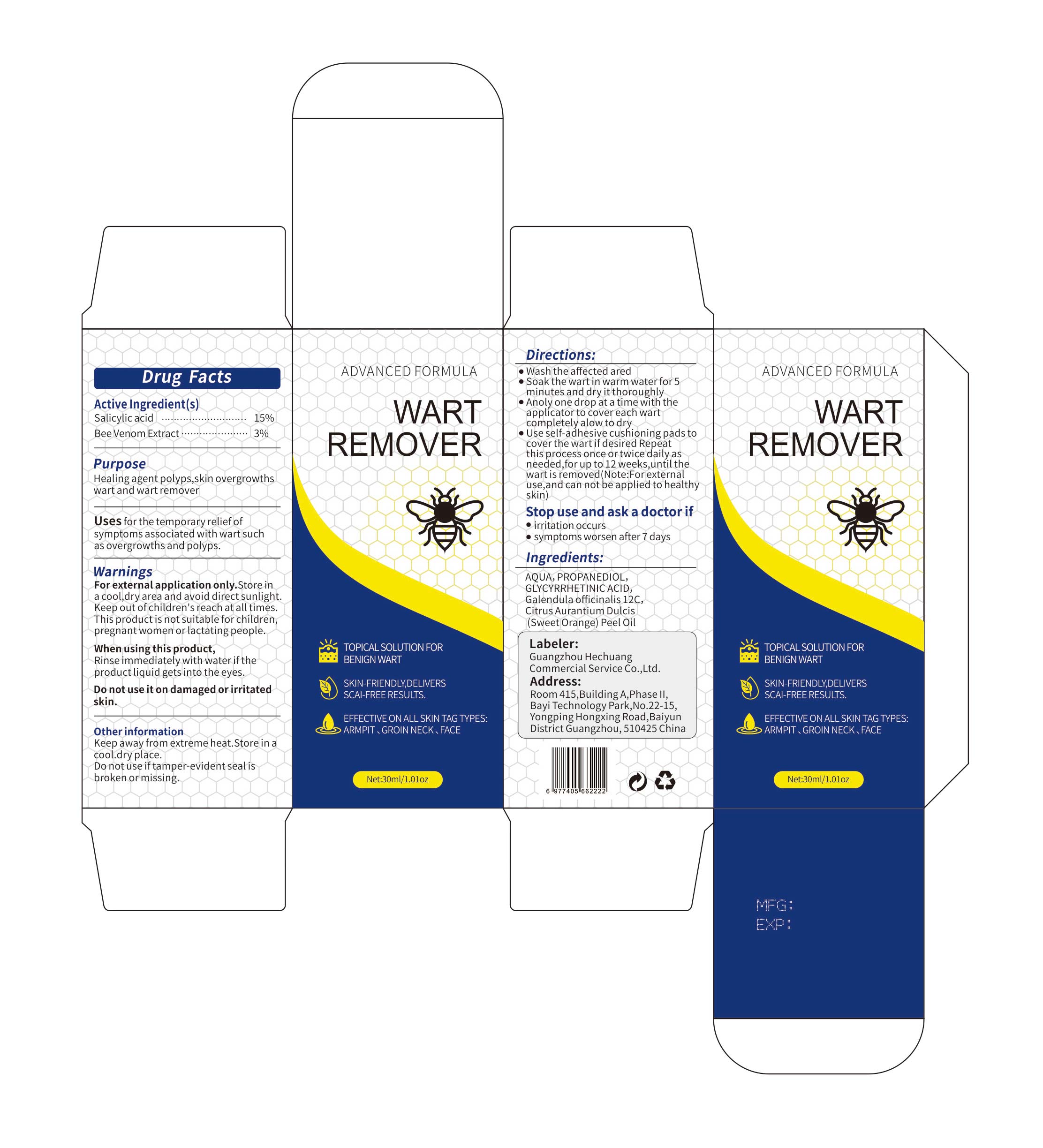 DRUG LABEL: Wart Remover
NDC: 87298-011 | Form: LIQUID
Manufacturer: Guangzhou Hechuang Commercial Service Co.,Ltd.
Category: otc | Type: HUMAN OTC DRUG LABEL
Date: 20251229

ACTIVE INGREDIENTS: BEE POLLEN 3 g/100 g; SALICYLIC ACID 15 g/100 g
INACTIVE INGREDIENTS: CHAMOMILE; PROPANEDIOL; GLYCYRRHETINIC ACID; ORANGE OIL; AQUA

Active Ingredient(s)

Salicylic acid 15%
Bee Venom Extract 3%

Purpose

Healing agent polyps,skin overgrowths wart and wart remover

Ingredients:

AQUA，PROPANEDIOL，GLYCYRRHETINIC ACID，Galendula officinalis 12C， Citrus Aurantium Dulcis (Sweet Orange) Peel Oil

Uses

Uses for the temporary relief of symptoms associated with wart such as overgrowths and polyps..

Stop use and ask a doctor if

●irritation occurs
●symptomms worsen after 7 days

Directions:

●Wash the affected ared
●Soak the wart in warm water for 5 minutes and dry it thoroughly
●Anoly one drop at a time with the applicator to cover each wart completely alow to dry
●Use self-adhesive cushioning pads to cover the wart if desired Repeat this process once or twice daily as needed,for up to 12 weeks,until the wart is removed(Note:For external use,and can not be applied to healthy

Keep out of reach of children

keep out of children's reach at all times.

Warnings

For external application only.Store in a cool,dry area and avoid direct sunlight.keep out of children's reach at all times.This product is not suitable for children,pregnant women or lactating people.

When using this product,Rinse immediately with water if the product liquid gets into the eyes.

Do not use it on damaged or irritated skin.

Other information

Keep away from extreme heta.Store in a cool..dry place.
Do not use if tamper-evident seal is brolen or missing.

DOSAGE &ADMINISTRATION SECTION

●Wash the affected ared
●Soak the wart in warm water for 5 minutes and dry it thoroughly
●Anoly one drop at a time with the applicator to cover each wart completely alow to dry
●Use self-adhesive cushioning pads to cover the wart if desired Repeat this process once or twice daily as needed,for up to 12 weeks,until the wart is removed(Note:For external use,and can not be applied to healthy